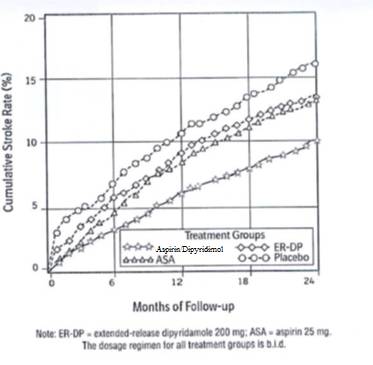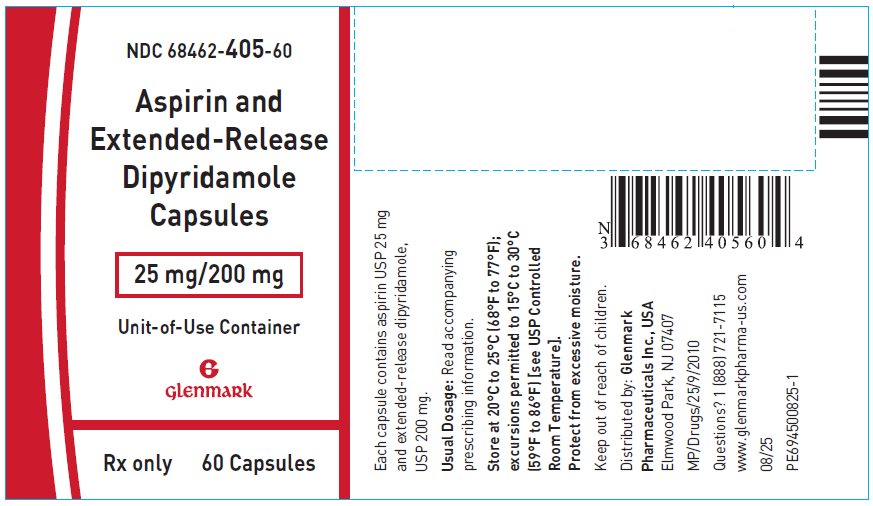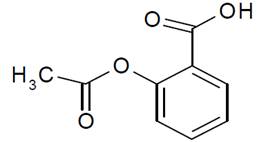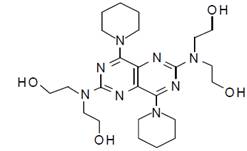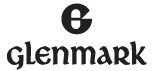 DRUG LABEL: ASPRIN AND EXTENDED-RELEASE DIPYRIDAMOLE
NDC: 68462-405 | Form: CAPSULE
Manufacturer: Glenmark Pharmaceuticals Inc., USA
Category: prescription | Type: HUMAN PRESCRIPTION DRUG LABEL
Date: 20260105

ACTIVE INGREDIENTS: ASPIRIN 25 mg/1 1; DIPYRIDAMOLE 200 mg/1 1
INACTIVE INGREDIENTS: ACACIA; METHACRYLIC ACID - METHYL METHACRYLATE COPOLYMER (1:2); GLYCERYL DIBEHENATE; HYPROMELLOSE PHTHALATE (31% PHTHALATE, 40 CST); HYPROMELLOSE, UNSPECIFIED; HYPROMELLOSE 2910 (3 MPA.S); HYPROMELLOSE 2910 (50 MPA.S); LACTOSE MONOHYDRATE; MICROCRYSTALLINE CELLULOSE; TALC; POVIDONE K30; SILICON DIOXIDE; TARTARIC ACID; TRIACETIN; FD&C BLUE NO. 1; FD&C RED NO. 3; FD&C RED NO. 40; FD&C YELLOW NO. 6; GELATIN, UNSPECIFIED; FERRIC OXIDE YELLOW; SODIUM LAURYL SULFATE; TITANIUM DIOXIDE; FERROSOFERRIC OXIDE; POTASSIUM HYDROXIDE; SHELLAC

HIGHLIGHTS OF PRESCRIBING INFORMATION

These highlights do not include all the information needed to use ASPIRIN and EXTENDED-RELEASE DIPYRIDAMOLE CAPSULES safely and effectively. See full prescribing information for ASPIRIN and EXTENDED-RELEASE DIPYRIDAMOLE CAPSULES.
ASPIRIN and extended-release DIPYRIDAMOLE capsules, for oral use
Initial U.S. Approval: 1999

1 INDICATIONS AND USAGE

- Aspirin and extended-release dipyridamole capsules are a combination of aspirin and dipyridamole, antiplatelet agents, indicated to reduce the risk of stroke in patients who have had transient ischemia of the brain or completed ischemic stroke due to thrombosis (1)

2 DOSAGE AND ADMINISTRATION

- One capsule twice daily (morning and evening) with or without food (2)
- In case of intolerable headaches during initial treatment, switch to one capsule at bedtime and low-dose aspirin in the morning; resume BID dosing within one week (2.1)
- Do not chew capsule (2)
- Not interchangeable with the individual components of aspirin and dipyridamole tablets (2)
- Dispense in this unit-of-use container (16)

3 DOSAGE FORMS AND STRENGTHS

- Capsule: 25 mg aspirin, USP/200 mg extended-release dipyridamole, USP (3)

4 CONTRAINDICATIONS

- Hypersensitivity to any product ingredients (4.1)
- Patients with known allergy to NSAIDs (4.2)
- Patients with the syndrome of asthma, rhinitis, and nasal polyps (4.2)

5 WARNINGS AND PRECAUTIONS

- Aspirin and extended-release dipyridamole capsules increase the risk of bleeding (5.1)
- Avoid use in patients with severe hepatic or renal insufficiency (5.2, 5.3)
- Interrupt aspirin and extended-release dipyridamole capsules 48 hours before using intravenous dipyridamole or other adenosinergic agents for stress testing (5.6, 7.1)

6 ADVERSE REACTIONS

- The most frequently reported adverse reactions (>10% and greater than placebo) were headache, dyspepsia, abdominal pain, nausea, and diarrhea (6.1)

To report SUSPECTED ADVERSE REACTIONS, contact Glenmark Pharmaceuticals Inc., USA at 1 (888) 721-7115 or FDA at 1-800-FDA-1088 or www.fda.gov/medwatch.

7 DRUG INTERACTIONS

- Co-administration with anticoagulants, antiplatelets, or NSAIDs can increase risk of bleeding (7.1)
- Decreased renal function can occur with co-administration with NSAIDs (7.1)

FULL PRESCRIBING INFORMATION

1 INDICATIONS AND USAGE

Aspirin and extended-release dipyridamole capsules are indicated to reduce the risk of stroke in patients who have had transient ischemia of the brain or completed ischemic stroke due to thrombosis.

2 DOSAGE AND ADMINISTRATION

Aspirin and extended-release dipyridamole capsules are not interchangeable with the individual components of aspirin and dipyridamole tablets.

The recommended dose of aspirin and extended-release dipyridamole capsules is one capsule given orally twice daily, one in the morning and one in the evening. Swallow capsules whole without chewing. Aspirin and extended-release dipyridamole capsules can be administered with or without food.

2.1 Alternative Regimen in Case of Intolerable Headaches

In the event of intolerable headaches during initial treatment, switch to one capsule at bedtime and low-dose aspirin in the morning. Because there are no outcome data with this regimen and headaches become less of a problem as treatment continues, patients should return to the usual regimen as soon as possible, usually within one week.

3 DOSAGE FORMS AND STRENGTHS

Aspirin and Extended-Release Dipyridamole Capsules, 25 mg/200 mg are available as size ‘0el’ empty hard gelatin capsules with a reddish brown opaque cap and a cream opaque body, imprinted with the Glenmark logo ‘G’ on the cap and ‘405’ on the body with black ink. The capsules are filled with light yellow to yellow colored dipyridamole pellets in extended-release form and a white to off-white aspirin tablet in immediate-release form.

4 CONTRAINDICATIONS

4.1 Hypersensitivity

Aspirin and extended-release dipyridamole capsules are contraindicated in patients with known hypersensitivity to any of the product components.

4.2 Allergy

Aspirin is contraindicated in patients with known allergy to nonsteroidal anti-inflammatory drug (NSAID) products and in patients with the syndrome of asthma, rhinitis, and nasal polyps. Aspirin may cause severe urticaria, angioedema or bronchospasm.

4.3 Reye Syndrome

Do not use aspirin in children or teenagers with viral infections because of the risk of Reye syndrome.

5 WARNINGS AND PRECAUTIONS

5.1 Risk of Bleeding

Aspirin and extended-release dipyridamole capsules increase the risk of bleeding. Risk factors for bleeding include the use of other drugs that increase the risk of bleeding (e.g., anticoagulants, antiplatelet agents, heparin, anagrelide, fibrinolytic therapy, and chronic use of NSAIDs) [see Drug Interaction (7.1)].

Intracranial Hemorrhage

In European Stroke Prevention Study-2 (ESPS2), the annualized event rate for intracranial hemorrhage was 0.39%/year in the Aspirin and extended-release dipyridamole capsules group, 0.26%/year in the extended-release dipyridamole (ER-DP) group, 0.24%/year in the aspirin (ASA) group, and 0.29%/year in the placebo groups.

Gastrointestinal (GI) Side Effects

GI side effects include stomach pain, heartburn, nausea, vomiting, and gross GI bleeding. Although minor upper GI symptoms, such as dyspepsia, are common and can occur anytime during therapy, physicians should remain alert for signs of ulceration and bleeding, even in the absence of previous GI symptoms. Inform patients about the signs and symptoms of GI side effects and what steps to take if they occur.

In ESPS2, the annualized event rate for gastrointestinal bleeding was 2.97%/year in the Aspirin and extended-release dipyridamole capsules group, 1.58%/year in the extended-release dipyridamole group, 2.06%/year in the aspirin group, and 1.40%/year in the placebo groups.

Peptic Ulcer Disease

Avoid using aspirin in patients with a history of active peptic ulcer disease, which can cause gastric mucosal irritation and bleeding.

Alcohol Warning

Because aspirin and extended-release dipyridamole capsules contain aspirin, counsel patients who consume three or more alcoholic drinks every day about the bleeding risks involved with chronic, heavy alcohol use while taking aspirin.

5.2 Renal Failure

Avoid aspirin in patients with severe renal failure (glomerular filtration rate less than 10 mL/minute) [see Use in specific Population (8.6) and Clinical Pharmacology (12.3)].

5.3 Hepatic Insufficiency

Elevations of hepatic enzymes and hepatic failure have been reported in association with dipyridamole administration [see Use in specific Population (8.6) and Clinical Pharmacology (12.3)].

5.4 Coronary Artery Disease

Dipyridamole has a vasodilatory effect. Chest pain may be precipitated or aggravated in patients with underlying coronary artery disease who are receiving dipyridamole.

For stroke or TIA patients for whom aspirin is indicated to prevent recurrent myocardial infarction (MI) or angina pectoris, the aspirin in this product may not provide adequate treatment for the cardiac indications.

5.5 Hypotension

Dipyridamole produces peripheral vasodilation, which can exacerbate pre-existing hypotension.

5.6 Stress Testing with Intravenous Dipyridamole and Other Adenosinergic Agents

Clinical experience suggests that patients being treated with aspirin and extended-release dipyridamole capsules who also require pharmacological stress testing with intravenous dipyridamole or other adenosinergic agents (e.g. adenosine, regadenoson) should interrupt aspirin and extended-release dipyridamole capsules for 48 hours prior to stress testing [see Drug Interactions (7.1)].

Intake of aspirin and extended-release dipyridamole capsules within 48 hours prior to stress testing with intravenous dipyridamole or other adenosinergic agents may increase the risk for cardiovascular side effects of these agents and may impair the sensitivity of the test.

5.7 General

Aspirin and extended-release dipyridamole capsules are not interchangeable with the individual components of aspirin and dipyridamole tablets.

6 ADVERSE REACTIONS

The following adverse reactions are discussed elsewhere in the labeling:

- Hypersensitivity [see Contraindications (4.1)]
- Allergy [see Contraindications (4.2)]
- Risk of Bleeding [see Warnings and Precautions (5.1)]

6.1 Clinical Trials Experience

Because clinical trials are conducted under widely varying conditions, adverse reaction rates observed in the clinical trials of a drug cannot be directly compared to rates in the clinical trials of another drug and may not reflect the rates observed in practice.

The efficacy and safety of aspirin and extended-release dipyridamole was established in the European Stroke Prevention Study-2 (ESPS2). ESPS2 was a double-blind, placebo-controlled study that evaluated 6602 patients over the age of 18 years who had a previous ischemic stroke or transient ischemic attack within ninety days prior to entry. Patients were randomized to either aspirin and extended-release dipyridamole, aspirin, ER-DP, or placebo [see Clinical Studies (14)]; primary endpoints included stroke (fatal or nonfatal) and death from all causes.

This 24-month, multicenter, double-blind, randomized study (ESPS2) was conducted to compare the efficacy and safety of aspirin and extended-release dipyridamole with placebo, extended-release dipyridamole alone and aspirin alone. The study was conducted in a total of 6602 male and female patients who had experienced a previous ischemic stroke or transient ischemia of the brain within three months prior to randomization.

Table 1 presents the annualized event rate for adverse events that occurred in 1%/year or more of patients treated with Aspirin and extended-release dipyridamole capsules where the incidence was also at least 1%/year greater than in those patients treated with placebo. There is no clear benefit of the dipyridamole/aspirin combination over aspirin with respect to safety.

Table 1 Incidence of Adverse Events in ESPS2a
 | Individual Treatment Group
Body System/Preferred Term | Aspirin and Extended-Release Dipyridamole n (%/year)b | ER-DP Alone n (%/year)b | ASA Alone n (%/year)b | Placebo n (%/year)b
Total Number of Patients | 1650 | 1654 | 1649 | 1649
Central and Peripheral Nervous System Disorders
Headache | 647 (28.25) | 634 (27.91) | 558 (22.10) | 543 (22.29)
Gastrointestinal System Disorders
Dyspepsia | 303 (13.23) | 288 (12.68) | 299 (11.84) | 275 (11.29)
Abdominal Pain | 289 (12.62) | 255 (11.22) | 262 (10.38) | 239 (9.81)
Nausea | 264 (11.53) | 254 (11.18) | 210 (8.32) | 232 (9.53)
Diarrhea | 210 (9.17) | 257 (11.31) | 112 (4.44) | 161 (6.61)
Vomiting | 138 (6.03) | 129 (5.68) | 101 (4) | 118 (4.84)
Platelet, Bleeding and Clotting Disorders
Hemorrhage NOS | 52 (2.27) | 24 (1.06) | 46 (1.82) | 24 (0.99)

a Reported by ≥1%/year of patients during Aspirin and extended-release dipyridamole capsules treatment where the incidence was at least 1%/year greater than in those treated with placebo.

b Annual event rate per 100 pt-years = 100* number of subjects with event/subject-years. Subject-years is defined as cumulative number of days on treatment divided by 365.25.

Note: ER-DP = extended-release dipyridamole 200 mg; ASA = aspirin 25 mg. The dosage regimen for all treatment groups is BID.

NOS = not otherwise specified.

Discontinuation due to adverse events in ESPS2 was 25% for aspirin and extended-release dipyridamole 25% for extended-release dipyridamole, 19% for aspirin, and 21% for placebo (refer to Table 2).

Table 2 Incidence of Adverse Events that Led to the Discontinuation of Treatmenta

 | Treatment Groups
 | Aspirin and Extended-Release Dipyridamole; n (%/year)b | ER-DP; n (%/year)b | ASA; n (%/year)b | Placebo; n (%/year)b
Total Number of Patients | 1650 | 1654 | 1649 | 1649
Patients with at least one Adverse Event that led to treatment discontinuation | 417 (18.21) | 419 (18.44) | 318 (12.59) | 352 (14.45)
Headache | 165 (7.20) | 166 (7.31) | 57 (2.26) | 69 (2.83)
Nausea | 91 (3.97) | 95 (4.18) | 51 (2.02) | 53 (2.18)
Abdominal Pain | 74 (3.23) | 64 (2.82) | 56 (2.22) | 52 (2.13)
Vomiting | 53 (2.31) | 52 (2.29) | 28 (1.11) | 24 (0.99)

a Reported by ≥1%/year of patients during Aspirin and Extended-Release Dipyridamole capsules treatment where the incidence was at least 1%/year greater than in those treated with placebo.

b Annual event rate per 100 pt-years = 100* number of subjects with event/subject-years. Subject-years is defined as cumulative number of days on treatment divided by 365.25.

Note: ER-DP = extended-release dipyridamole 200 mg; ASA = aspirin 25 mg. The dosage regimen for all treatment groups is BID.

Headache was most notable in the first month of treatment.

6.2 Post-Marketing Experience

The following is a list of additional adverse reactions that have been reported either in the literature or are from post-marketing spontaneous reports for either dipyridamole or aspirin. Because these reactions are reported voluntarily from a population of uncertain size, it is not always possible to estimate reliably their frequency or establish a causal relationship to drug exposure. Decisions to include these reactions in labeling are typically based on one or more of the following factors: (1) seriousness of the reaction, (2) frequency of reporting, or (3) strength of causal connection to Aspirin and extended-release dipyridamole capsules.

Body as a Whole: Hypothermia, chest pain, allergic reaction, syncope

Cardiovascular: Angina pectoris, hypotension

Central Nervous System: Cerebral edema, dizziness, cerebral hemorrhage, intracranial hemorrhage, subarachnoid hemorrhage

Fluid and Electrolyte: Hyperkalemia, metabolic acidosis, respiratory alkalosis, hypokalemia

Gastrointestinal: Pancreatitis, Reye syndrome, hematemesis, gastritis, ulceration and perforation, hemorrhage rectum, melena, GI hemorrhage

Hearing and Vestibular Disorders: Hearing loss

Heart Rate and Rhythm Disorders: Tachycardia, palpitation

Immune System Disorders: Hypersensitivity, acute anaphylaxis, laryngeal edema

Liver and Biliary System Disorders: Hepatitis, hepatic failure, cholelithiasis, jaundice, hepatic function abnormal

Musculoskeletal: Rhabdomyolysis, myalgia

Metabolic and Nutritional Disorders: Hypoglycemia, dehydration

Platelet, Bleeding and Clotting Disorders: Prolongation of the prothrombin time, disseminated intravascular coagulation, coagulopathy, thrombocytopenia, hematoma, gingival bleeding, epistaxis, purpura

Psychiatric Disorders: Confusion, agitation

Respiratory: Tachypnea, dyspnea, hemoptysis

Skin and Appendages Disorders: Rash, alopecia, angioedema, Stevens-Johnson syndrome, skin hemorrhages such as bruising, ecchymosis, and hematoma, pruritus, urticaria, and drug reaction with eosinophilia and systemic symptoms (DRESS)

Urogenital: Interstitial nephritis, papillary necrosis, proteinuria, renal insufficiency and failure, hematuria

Vascular (Extracardiac) Disorders: Allergic vasculitis, flushing

Other Adverse Events: Anorexia, aplastic anemia, migraine, pancytopenia, thrombocytosis.

7 DRUG INTERACTIONS

7.1 Drug Interaction Study Information Obtained From Literature

Adenosinergic agents (e.g. adenosine, regadenoson)

Dipyridamole has been reported to increase the plasma levels and cardiovascular effects of adenosine. Adjustment of adenosine dosage may be necessary. Dipyridamole also increases the cardiovascular effects of regadenoson, an adenosine A2A-receptor agonist. The potential risk of cardiovascular side effects with intravenous adenosinergic agents may be increased during the testing period when dipyridamole is not held 48 hours prior to stress testing.

Angiotensin Converting Enzyme (ACE) Inhibitors

Because of the indirect effect of aspirin on the renin-angiotensin conversion pathway, the hyponatremic and hypotensive effects of ACE inhibitors may be diminished by concomitant administration of aspirin.

Acetazolamide

Concurrent use of aspirin and acetazolamide can lead to high serum concentrations of acetazolamide (and toxicity) due to competition at the renal tubule for secretion.

Anticoagulants and Antiplatelets

Patients taking Aspirin and extended-release dipyridamole capsules in combination with anticoagulants, antiplatelets, or any substance impacting coagulation are at increased risk for bleeding. Aspirin can displace warfarin from protein binding sites, leading to prolongation of both the prothrombin time and the bleeding time. Aspirin can increase the anticoagulant activity of heparin, increasing bleeding risk.

Anagrelide

Patients taking aspirin in combination with anagrelide are at an increased risk of bleeding.

Anticonvulsants

Salicylic acid can displace protein-bound phenytoin and valproic acid, leading to a decrease in the total concentration of phenytoin and an increase in serum valproic acid levels.

Beta Blockers

The hypotensive effects of beta blockers may be diminished by the concomitant administration of aspirin due to inhibition of renal prostaglandins, leading to decreased renal blood flow and salt and fluid retention.

Cholinesterase Inhibitors

Dipyridamole may counteract the anticholinesterase effect of cholinesterase inhibitors, thereby potentially aggravating myasthenia gravis.

Diuretics

The effectiveness of diuretics in patients with underlying renal or cardiovascular disease may be diminished by the concomitant administration of aspirin due to inhibition of renal prostaglandins, leading to decreased renal blood flow and salt and fluid retention.

Methotrexate

Salicylate can inhibit renal clearance of methotrexate, leading to bone marrow toxicity, especially in the elderly or renal impaired.

Nonsteroidal Anti-Inflammatory Drugs (NSAIDs)

The concurrent use of aspirin with other NSAIDs may increase bleeding or lead to decreased renal function.

Oral Hypoglycemics

Moderate doses of aspirin may increase the effectiveness of oral hypoglycemic drugs, leading to hypoglycemia.

Uricosuric Agents (probenecid and sulfinpyrazone)

Salicylates antagonize the uricosuric action of uricosuric agents.

8 USE IN SPECIFIC POPULATIONS

8.1 Pregnancy

Risk Summary

Available data from published studies and postmarketing experience with Aspirin and extended-release dipyridamole capsules use during pregnancy have not identified a clear association between Aspirin and extended-release dipyridamole capsules use and major birth defects, miscarriage, or adverse maternal or fetal outcomes (see Data). Aspirin and extended-release dipyridamole capsules contains low-dose aspirin which is an NSAID (see Clinical Considerations). In animal reproduction studies, there were adverse developmental effects with administration of aspirin in rats and rabbits at doses about 66 and 44 times, respectively, the human exposure at the maximum recommended daily dose of aspirin-dipyridamole. Reproduction studies with dipyridamole in mice, rabbits, and rats have revealed no evidence of harm to the fetus up to doses about 25 times the maximum recommended daily human dose of aspirin-dipyridamole. Nonclinical data are suggestive of a possible potentiation of aspirin-related fetal toxicity when combined with dipyridamole (see Data).

The estimated background risk of major birth defects and miscarriage for the indicated population is unknown. All pregnancies have a background risk of birth defect, loss, or other adverse outcomes. In the U.S. general population, the estimated background risk of major birth defects and miscarriage in clinically recognized pregnancies is 2 to 4 and 15 to 20%, respectively.

Clinical Considerations

Labor and Delivery

Aspirin and extended-release dipyridamole capsules, which contains dipyridamole and low-dose aspirin, increases the risk for bleeding [see Warning and Precautions (5.1)]. Maternal use of high-dose aspirin can result in excessive blood loss at delivery, prolonged gestation, prolonged labor, intracranial hemorrhage in premature infants, low birth weight, stillbirth, and neonatal death.

Data

Human Data

Published data from clinical trials, observational studies, case series, and case reports over several decades have not identified a clear association between aspirin-dipyridamole use in pregnancy and major birth defects, miscarriage, or adverse maternal or fetal outcomes. However, these studies cannot definitively establish the absence of any aspirin-dipyridamole associated risks. Methodological limitations of these studies include variability in the timing and dose of drug exposure (e.g., most exposures occurred beyond the first trimester) and the small sample sizes of individual studies.

Animal Data

Aspirin has been shown to be teratogenic in rats (spina bifida, exencephaly, microphthalmia and coelosomia) and rabbits (congested fetuses, agenesis of skull and upper jaw, generalized edema with malformation of the head, and diaphanous skin) at oral doses of 330 mg/kg/day and 110 mg/kg/day, respectively. These doses, which also resulted in a high resorption rate in rats (63% of implantations versus 5% in controls), are, on a mg/m^2 basis, about 66 and 44 times, respectively, the dose of aspirin contained in the maximum recommended daily human dose of aspirin-dipyridamole. Reproduction studies with dipyridamole have been performed in mice, rabbits and rats at oral doses of up to 125 mg/kg, 40 mg/kg, and 1000 mg/kg, respectively (about 1½, 2, and 25 times the maximum recommended daily human oral dose, respectively, on a mg/m^2 basis) and have revealed no evidence of harm to the fetus due to dipyridamole. When 330 mg aspirin/kg/day was combined with 75 mg dipyridamole/kg/day in the rat at doses about 66 and 2 times, respectively, the maximum recommended daily human dose, the resorption rate approached 100%.

8.2 Lactation

Risk Summary

Based on data from a clinical lactation study in breastfeeding women taking low-dose aspirin, the metabolite salicylic acid is present in human milk in low levels (see Data). Dipyridamole is also present in human milk. There is no information on the effects of Aspirin and extended-release dipyridamole capsules or dipyridamole on the breastfed infant or on milk production. There is insufficient information to determine the effects of aspirin on the breastfed infant and no information on the effects of aspirin on milk production. The developmental and health benefits of breastfeeding should be considered along with the mother’s clinical need for Aspirin and extended-release dipyridamole capsules and any potential adverse effects on the breastfed child from Aspirin and extended-release dipyridamole capsules or from the underlying maternal condition.

Data

A published clinical study involved six exclusively breastfeeding women at 1 to 8 months postpartum who were taking 81 mg aspirin daily. Milk samples were collected at steady state, at 0, 1, 2, 4, 8, 12, and 24 hours after taking a dose of aspirin. Aspirin was undetectable in human milk. Salicylic acid was present in milk at low levels (average concentration of 24 ng/mL). Based on an average milk consumption of 150 mL/kg/day, the calculated relative infant dose was 0.4%. No adverse effects on the breastfed infants were noted.

8.4 Pediatric Use

Safety and effectiveness of Aspirin and extended-release dipyridamole capsules in pediatric patients have not been studied. Because of the aspirin component, use of this product in the pediatric population is not recommended [see Contraindications (4.3)].

8.5 Geriatric Use

Of the total number of subjects in ESPS2, 61% were 65 and over, while 27% were 75 and over. No overall differences in safety or effectiveness were observed between these subjects and younger subjects, and other reported clinical experience has not identified differences in responses between the elderly and younger patients, but greater sensitivity of some older individuals cannot be ruled out [see Clinical Pharmacology (12.3)].

8.6 Patients with Severe Hepatic or Severe Renal Dysfunction

Aspirin and extended-release dipyridamole capsules has not been studied in patients with hepatic or renal impairment. Avoid using aspirin containing products, such as Aspirin and extended-release dipyridamole capsules, in patients with severe hepatic or severe renal (glomerular filtration rate <10 mL/min) dysfunction [see Warnings and Precautions (5.2, 5.3) and Clinical Pharmacology (12.3)].

10 OVERDOSAGE

Because of the dose ratio of dipyridamole to aspirin, overdosage of aspirin and extended-release dipyridamole capsules are likely to be dominated by signs and symptoms of dipyridamole overdose. In case of real or suspected overdose, seek medical attention or contact a Poison Control Center immediately. Careful medical management is essential.

Based upon the known hemodynamic effects of dipyridamole, symptoms such as warm feeling, flushes, sweating, restlessness, feeling of weakness, and dizziness may occur. A drop in blood pressure and tachycardia might also be observed.

Salicylate toxicity may result from acute ingestion (overdose) or chronic intoxication. Severity of aspirin intoxication is determined by measuring the blood salicylate level. The early signs of salicylic overdose (salicylism), including tinnitus (ringing in the ears), occur at plasma concentrations approaching 200 mcg/mL. In severe cases, hyperthermia and hypovolemia are the major immediate threats to life. Plasma concentrations of aspirin above 300 mcg/mL are clearly toxic. Severe toxic effects are associated with levels above 400 mcg/mL. A single lethal dose of aspirin in adults is not known with certainty but death may be expected at 30 g.

Treatment of overdose consists primarily of supporting vital functions, increasing drug elimination, and correcting acid-base disturbances. Consider gastric emptying and/or lavage as soon as possible after ingestion, even if the patient has vomited spontaneously. After lavage and/or emesis, administration of activated charcoal as a slurry may be beneficial if less than 3 hours have passed since ingestion. Charcoal absorption should not be employed prior to emesis and lavage. Follow acid-base status closely with serial blood gas and serum pH measurements. Maintain fluid and electrolyte balance. Administer replacement fluid intravenously and augment with correction of acidosis. Treatment may require the use of a vasopressor. Infusion of glucose may be required to control hypoglycemia.

Administration of xanthine derivatives (e.g., aminophylline) may reverse the vasodilatory effects of dipyridamole overdose. Plasma electrolytes and pH should be monitored serially to promote alkaline diuresis of salicylate if renal function is normal. In patients with renal insufficiency or in cases of life-threatening intoxication, dialysis is usually required to treat salicylic overdose; however, since dipyridamole is highly protein bound, dialysis is not likely to remove dipyridamole. Exchange transfusion may be indicated in infants and young children.

11 DESCRIPTION

Aspirin and Extended-Release Dipyridamole Capsules are a combination of aspirin and dipyridamole, antiplatelet agents, intended for oral administration. Each hard gelatin capsule contains 200 mg dipyridamole, USP in an extended-release form and 25 mg aspirin, USP as an immediate-release sugar-coated tablet. In addition, each capsule contains the following inactive ingredients: acacia milled powder, eudragit S-100, glyceryl behenate, hydroxy propyl methyl cellulose phthalate HP-55, hypromellose, hypromellose E3LV, hypromellose E50LV, lactose monohydrate, microcrystalline cellulose, micronized talc, povidone K 30, silicon dioxide, talc, tartatic acid pellets and triacetin.

Each capsule shell contains FD & C blue 1, FD & C red 3, FD & C red 40, FD & C yellow 6, gelatin, iron oxide yellow, sodium lauryl sulphate and titanium dioxide.

The imprinting ink contains black iron oxide, potassium hydroxide, and shellac.

Dipyridamole

Dipyridamole is an antiplatelet agent chemically described as 2,2',2'',2'''-[(4,8-Dipiperidinopyrimido[5,4-d]pyrimidine-2,6-diyl)dinitrilo]-tetraethanol. It has the following structural formula:

Molecular formula: C24H40N8O4 Mol. Wt. 504.63 g/mol

Dipyridamole is an odorless yellow crystalline substance, having a bitter taste. It is soluble in dilute acids, methanol and chloroform, and is practically insoluble in water.

Aspirin

The antiplatelet agent aspirin (acetylsalicylic acid) is chemically known as benzoic acid, 2- (acetyloxy)-, and has the following structural formula:

Molecular formula: C9H8O4 Mol. Wt. 180.16 g/mol

Aspirin has white crystals, commonly tubular or needle-like, or white, crystalline powder. When exposed to moisture, aspirin hydrolyzes into salicylic and acetic acids, and gives off a vinegary odor. It is slightly soluble in water; freely soluble in alcohol; soluble in chloroform and in ether; sparingly soluble in absolute ether.

12 CLINICAL PHARMACOLOGY

12.1 Mechanism of Action

The antithrombotic action of Aspirin and extended-release dipyridamole capsules is the result of the additive antiplatelet effects of dipyridamole and aspirin.

Dipyridamole

Dipyridamole inhibits the uptake of adenosine into platelets, endothelial cells and erythrocytes in vitro and in vivo; the inhibition occurs in a dose-dependent manner at therapeutic concentrations (0.5 to 1.9 mcg/mL). This inhibition results in an increase in local concentrations of adenosine which acts on the platelet A2-receptor thereby stimulating platelet adenylate cyclase and increasing platelet cyclic-3',5'-adenosine monophosphate (cAMP) levels. Via this mechanism, platelet aggregation is inhibited in response to various stimuli such as platelet activating factor (PAF), collagen and adenosine diphosphate (ADP).

Dipyridamole inhibits phosphodiesterase (PDE) in various tissues. While the inhibition of cAMP-PDE is weak, therapeutic levels of dipyridamole inhibit cyclic-3', 5’- guanosine monophosphate-PDE (cGMP-PDE), thereby augmenting the increase in cGMP produced by EDRF (endothelium-derived relaxing factor, now identified as nitric oxide).

Aspirin

Aspirin inhibits platelet aggregation by irreversible inhibition of platelet cyclooxygenase and thus inhibits the generation of thromboxane A2, a powerful inducer of platelet aggregation and vasoconstriction.

12.2 Pharmacodynamics

The effect of either agent on the other's inhibition of platelet reactivity has not been evaluated.

12.3 Pharmacokinetics

There are no significant interactions between aspirin and dipyridamole. The kinetics of the components are unchanged by their co-administration as Aspirin and extended-release dipyridamole capsules.

Absorption

Dipyridamole:

Peak plasma levels of dipyridamole are achieved 2 hours (range 1 to 6 hours) after administration of a daily dose of 400 mg Aspirin and extended-release dipyridamole capsules (given as 200 mg BID). The peak plasma concentration at steady-state is 1.98 mcg/mL (1.01 to 3.99 mcg/mL) and the steady-state trough concentration is 0.53 mcg/mL (0.18 to 1.01 mcg/mL).

Aspirin:

Peak plasma levels of aspirin are achieved 0.63 hours (0.5 to 1 hour) after administration of a 50 mg aspirin daily dose from Aspirin and extended-release dipyridamole capsules (given as 25 mg BID). The peak plasma concentration at steady-state is 319 ng/mL (175 to 463 ng/mL). Aspirin undergoes moderate hydrolysis to salicylic acid in the liver and the gastrointestinal wall, with 50% to 75% of an administered dose reaching the systemic circulation as intact aspirin.

Effect of Food

Dipyridamole:

When Aspirin and extended-release dipyridamole capsules were taken with a high fat meal, dipyridamole peak plasma levels (Cmax) and total absorption (AUC) were decreased at steady-state by 20 to 30% compared to fasting. Due to the similar degree of inhibition of adenosine uptake at these plasma concentrations, this food effect is not considered clinically relevant.

Aspirin:

When Aspirin and extended-release dipyridamole capsules were taken with a high fat meal, there was no difference for aspirin in AUC at steady-state, and the approximately 50% decrease in Cmax was not considered clinically relevant based on a similar degree of cyclooxygenase inhibition comparing the fed and fasted state.

Distribution

Dipyridamole:

Dipyridamole is highly lipophilic (log P=3.71, pH=7); however, it has been shown that the drug does not cross the blood-brain barrier to any significant extent in animals. The steady-state volume of distribution of dipyridamole is about 92 L. Approximately 99% of dipyridamole is bound to plasma proteins, predominantly to alpha 1-acid glycoprotein and albumin.

Aspirin:

Aspirin is poorly bound to plasma proteins and its apparent volume of distribution is low (10 L). Its metabolite, salicylic acid, is highly bound to plasma proteins, but its binding is concentration-dependent (nonlinear). At low concentrations (<100 mcg/mL), approximately 90% of salicylic acid is bound to albumin. Salicylic acid is widely distributed to all tissues and fluids in the body, including the central nervous system, breast milk, and fetal tissues. Early signs of salicylate overdose (salicylism), including tinnitus (ringing in the ears), occur at plasma concentrations approximating 200 mcg/mL [see Overdosage (10)].

Metabolism and Elimination

Dipyridamole:

Dipyridamole is metabolized in the liver, primarily by conjugation with glucuronic acid, of which monoglucuronide which has low pharmacodynamic activity is the primary metabolite. In plasma, about 80% of the total amount is present as parent compound and 20% as monoglucuronide. Most of the glucuronide metabolite (about 95%) is excreted via bile into the feces, with some evidence of enterohepatic circulation. Renal excretion of parent compound is negligible and urinary excretion of the glucuronide metabolite is low (about 5%). With intravenous (i.v.) treatment of dipyridamole, a triphasic profile is obtained: a rapid alpha phase, with a half-life of about 3.4 minutes, a beta phase, with a half-life of about 39 minutes, (which, together with the alpha phase accounts for about 70% of the total area under the curve, AUC) and a prolonged elimination phase λz with a half-life of about 15.5 hours. Because of the extended absorption phase of the dipyridamole component, only the terminal phase is apparent from oral treatment with Aspirin and extended-release dipyridamole capsules which was 13.6 hours.

Aspirin:

Aspirin is rapidly hydrolyzed in plasma to salicylic acid, with a half-life of 20 minutes. Plasma levels of aspirin are essentially undetectable 2 to 2.5 hours after dosing and peak salicylic acid concentrations occur 1 hour (range: 0.5 to 2 hours) after administration of aspirin. Salicylic acid is primarily conjugated in the liver to form salicyluric acid, a phenolic glucuronide, an acyl glucuronide, and a number of minor metabolites. Salicylate metabolism is saturable and total body clearance decreases at higher serum concentrations due to the limited ability of the liver to form both salicyluric acid and phenolic glucuronide. Following toxic doses (10 to 20 g), the plasma half-life may be increased to over 20 hours.

The elimination of acetylsalicylic acid follows first-order kinetics with Aspirin and extended-release dipyridamole capsules and has a half-life of 0.33 hours. The half-life of salicylic acid is 1.71 hours. Both values correspond well with data from the literature at lower doses which state a resultant half-life of approximately 2 to 3 hours. At higher doses, the elimination of salicylic acid follows zero-order kinetics (i.e., the rate of elimination is constant in relation to plasma concentration), with an apparent half-life of 6 hours or higher. Renal excretion of unchanged drug depends upon urinary pH. As urinary pH rises above 6.5, the renal clearance of free salicylate increases from <5% to >80%. Alkalinization of the urine is a key concept in the management of salicylate overdose [see Overdosage (10).]. Following therapeutic doses, about 10% is excreted as salicylic acid and 75% as salicyluric acid, as the phenolic and acyl glucuronides, in urine.

Specific Populations

Geriatric Patients:

Dipyridamole:

In ESPS2 [see Clinical Studies (14)], plasma concentrations (determined as AUC) of dipyridamole in healthy elderly subjects (>65 years) were about 40% higher than in subjects younger than 55 years receiving treatment with Aspirin and extended-release dipyridamole capsules.

Hepatic Dysfunction:

No study has been conducted with Aspirin and extended-release dipyridamole capsules in patients with hepatic dysfunction.

Dipyridamole:

In a study conducted with an intravenous formulation of dipyridamole, patients with mild to severe hepatic insufficiency showed no change in plasma concentrations of dipyridamole but showed an increase in the pharmacologically inactive monoglucuronide metabolite. Dipyridamole can be dosed without restriction as long as there is no evidence of hepatic failure.

Aspirin:

Avoid aspirin in patients with severe hepatic insufficiency.

Renal Dysfunction: Dipyridamole: In ESPS2 patients [see Clinical Studies (14)], with creatinine clearances ranging from about 15 mL/min to >100 mL/min, no changes were observed in the pharmacokinetics of dipyridamole or its glucuronide metabolite if data were corrected for differences in age.

Aspirin:

Avoid aspirin in patients with severe renal failure (glomerular filtration rate <10 mL/min).

Drug Interaction Studies A dedicated drug interaction study was conducted in 60 healthy volunteers to evaluate the effects of omeprazole 80 mg administered once daily on the pharmacokinetics (PK) of dipyridamole and the pharmacodynamics (PD) of acetylsalicylic acid when co-administered with Aspirin and extended-release dipyridamole capsules twice daily. Dipyridamole exposure (Cmax and AUC) at steady-state were similar with or without omeprazole co-administration. The pharmacokinetics of acetylsalicylic acid was not characterized. However, the antiplatelet activity as measured by arachidonic acid induced platelet aggregation was similar between the treatment arms at steady-state.

13 NONCLINICAL TOXICOLOGY

13.1 Carcinogenesis, Mutagenesis, Impairment of Fertility

In studies in which dipyridamole was administered in the feed to mice (up to 111 weeks in males and females) and rats (up to 128 weeks in males and up to 142 weeks in females), there was no evidence of drug-related carcinogenesis. The highest dose administered in these studies (75 mg/kg/day) was, on a mg/m^2 basis, about equivalent to the maximum recommended daily human oral dose (MRHD) in mice and about twice the MRHD in rats.

Combinations of dipyridamole and aspirin (1:5 ratio) tested negative in the Ames test, in vivo chromosome aberration tests (in mice and hamsters), oral micronucleus tests (in mice and hamsters) and oral dominant lethal test (in mice). Aspirin, alone, induced chromosome aberrations in cultured human fibroblasts. Mutagenicity tests of dipyridamole alone with bacterial and mammalian cell systems were negative.

Combinations of dipyridamole and aspirin have not been evaluated for effects on fertility and reproductive performance. There was no evidence of impaired fertility when dipyridamole was administered to male and female rats at oral doses up to 500 mg/kg/day (about 12 times the MRHD on a mg/m^2 basis). A significant reduction in number of corpora lutea with consequent reduction in implantations and live fetuses was, however, observed at 1250 mg/kg (more than 30 times the MRHD on a mg/m^2 basis). Aspirin inhibits ovulation in rats.

14 CLINICAL STUDIES

ESPS2 (European Stroke Prevention Study-2) was a double-blind, placebo-controlled, 24-month study in which 6602 patients over the age of 18 years had an ischemic stroke (76%) or transient ischemic attack (TIA, 24%) within three months prior to entry. Patients were enrolled in 13 European countries between February 1989 and May 1995 and were randomized to one of four treatment groups: Aspirin and extended-release dipyridamole 25 mg/200 mg; extended-release dipyridamole (ER-DP) 200 mg alone; aspirin (ASA) 25 mg alone; or placebo. The mean age in this population was 66.7 years with 58% of them being males. Patients received one capsule twice daily (morning and evening). Efficacy assessments included analyses of stroke (fatal or nonfatal) and death (from all causes) as confirmed by a blinded morbidity and mortality assessment group. There were no differences with regard to efficacy based on age or gender; patients who were older had a trend towards more events.

Stroke Endpoint

Aspirin and extended-release dipyridamole reduced the risk of stroke by 22.1% compared to aspirin 50 mg/day alone (p = 0.008) and reduced the risk of stroke by 24.4% compared to extended-release dipyridamole 400 mg/day alone (p = 0.002) (Table 3). Aspirin and extended-release dipyridamole reduced the risk of stroke by 36.8% compared to placebo (p <0.001).

Table 3 Summary of First Stroke (Fatal or Nonfatal): ESPS2: Intent-to-Treat Population
 | Total Number of Patients n | Number of Patients With Stroke Within 2 Years n (%) | Kaplan-Meier Estimate of Survival at 2 Years (95% C.I.) | Gehan- Wilcoxon Test P-value | Risk Reduction at 2 Years | Odds Ratio (95% C.I.)
Individual Treatment Group
Aspirin and extended-release dipyridamole | 1650 | 157 (9.5%) | 89.9% (88.4%, 91.4%) | - | - | -
ER-DP | 1654 | 211 (12.8%) | 86.7% (85%, 88.4%) | - | - | -
ASA | 1649 | 206 (12.5%) | 87.1% (85.4%, 88.7%) | - | - | -
Placebo | 1649 | 250 (15.2%) | 84.1% (82.2%, 85.9%) | - | - | -
Pairwise Treatment Group Comparisons
Aspirin and extended-release dipyridamole vs. ER-DP | - | - | - | 0.002b | 24.4% | 0.72 (0.58, 0.90)
Aspirin and extended-release dipyridamole vs. ASA | - | - | - | 0.008b | 22.1% | 0.74 (0.59, 0.92)
Aspirin and extended-release dipyridamole vs. Placebo | - | - | - | <0.001b | 36.8% | 0.59 (0.48, 0.73)
ER-DP vs. Placebo | - | - | - | 0.036a | 16.5% | 0.82 (0.67, 1)
ASA vs. Placebo | - | - | - | 0.009b | 18.9% | 0.80 (0.66, 0.97)
a0.010 <p-value ≤0.050; bp-value ≤0.010.
Note: ER-DP = extended-release dipyridamole 200 mg; ASA = aspirin 25 mg. The dosage regimen for all treatment groups is BID.

Figure 1 ESPS2: Cumulative Stroke Rate (Fatal or Nonfatal)

Over 24 months of Follow-Up

Combined Stroke or Death Endpoint

In ESPS2, Aspirin and extended-release dipyridamole capsules reduced the risk of stroke or death by 24.2% compared to placebo.

Aspirin and extended-release dipyridamole capsules reduced the risk of stroke or death by 12.1% compared to aspirin alone and by 10.3% compared to extended-release dipyridamole alone. These results were not statistically significant.

Death Endpoint

The incidence rate of all-cause mortality was 11.3% for Aspirin and extended-release dipyridamole capsules, 11% for aspirin alone, 11.4% for extended-release dipyridamole alone and 12.3% for placebo alone. The differences between the Aspirin and extended-release dipyridamole capsules, aspirin alone and extended-release dipyridamole alone treatment groups were not statistically significant. These incidence rates for Aspirin and extended-release dipyridamole capsules and aspirin alone are consistent with previous aspirin studies in stroke and TIA patients.

16 HOW SUPPLIED/STORAGE AND HANDLING

Aspirin and Extended-Release Dipyridamole Capsules, 25 mg/200 mg are available as size ‘0el’ empty hard gelatin capsules with a reddish brown opaque cap and a cream opaque body, imprinted with the Glenmark logo ‘G’ on the cap and ‘405’ on the body with black ink. The capsules are filled with light yellow to yellow colored dipyridamole pellets in extended-release form and a white to off-white aspirin tablet in immediate-release form.

Aspirin and Extended-Release Dipyridamole Capsules, 25 mg/200 mg are supplied in unit-of-use bottles of 30 capsules (NDC 68462-405-30) and unit-of-use bottles of 60 capsules (NDC 68462-405-60).

Store at 20°C to 25°C (68°F to 77°F); excursions permitted to 15°C to 30°C (59°F to 86°F) [see USP Controlled Room Temperature]. Protect from excessive moisture.

17 PATIENT COUNSELING INFORMATION

Advise the patient to read the FDA-approved patient labeling (Patient Information).

- Risk of Bleeding

Inform patients that as with other antiplatelet agents, there is a general risk of bleeding including intracranial and gastrointestinal bleeding. Inform patients about the signs and symptoms of bleeding, including occult bleeding. Tell patients to notify their physician if they are prescribed any drug which may increase risk of bleeding.

Counsel patients who consume three or more alcoholic drinks daily about the bleeding risks involved with chronic, heavy alcohol use while taking aspirin.

- Pregnancy

Advise patients to notify their healthcare provider if they become pregnant or intend to become pregnant during treatment with Aspirin and extended-release dipyridamole capsules [see Use in Specific Population (8.1)].

- Headaches

Some patients may experience headaches upon treatment initiation; these are usually transient. In case of intolerable headaches, tell patients to contact their physician.

- Stress Test

Instruct patients who are scheduled to undergo a pharmacologic stress test to tell their healthcare provider that they are taking aspirin and extended-release dipyridamole capsules.

- Dosage and Administration

Tell patients that aspirin and extended-release dipyridamole capsules should be swallowed whole, and not chewed or crushed. If you miss a dose, continue with your next dose on your regular schedule. Do not take a double dose.

- Storage

Inform patients to protect aspirin and extended-release dipyridamole capsules from moisture.

Distributed by:

Glenmark Pharmaceuticals Inc., USA

Elmwood Park, NJ 07407

Questions? 1 (888) 721-7115

www.glenmarkpharma-us.com

September 2025

Patient Information

Aspirin (AS-pir-in) and Extended-Release Dipyridamole (dye-pir-ID-a-mole) Capsules

Read this Patient Information before you start taking aspirin and extended-release dipyridamole capsules and each time you get a refill. There may be new information. This information does not take the place of talking to your healthcare provider about your medical condition or your treatment.

What are Aspirin and Extended-Release Dipyridamole Capsules?

Aspirin and extended-release dipyridamole capsules are a prescription medicine that contains aspirin and a medicine that is slowly released in your body, called dipyridamole. Aspirin and extended-release dipyridamole capsules are used to lower the risk of stroke in people who have had a "mini-stroke" (transient ischemic attack or TIA) or stroke due to a blood clot.

It is not known if aspirin and extended-release dipyridamole capsules are safe and effective in children. See “Who should not take aspirin and extended-release dipyridamole capsules?”

Who should not take Aspirin and Extended-Release Dipyridamole Capsules?

Do not take Aspirin and Extended-Release Dipyridamole Capsules if you:

- are allergic to any of the ingredients in aspirin and extended-release dipyridamole capsules. See the end of this leaflet for a list of ingredients in aspirin and extended-release dipyridamole capsules.
- are allergic to non-steroidal anti-inflammatory drugs (NSAIDs)
- have asthma in combination with runny nose and nasal polyps

Do not give aspirin and extended-release dipyridamole capsules to a child or teenager with a viral illness. Reye syndrome, a life-threatening condition, can happen when aspirin (an ingredient in aspirin and extended-release dipyridamole capsules) is used in children and teenagers who have certain viral illnesses.

What should I tell my doctor before using Aspirin and Extended-Release Dipyridamole Capsules?

Before taking Aspirin and Extended-Release Dipyridamole Capsules, tell your healthcare provider if you:

- have stomach ulcers
- have a history of bleeding problems
- have heart problems
- have kidney or liver problems
- have low blood pressure
- have myasthenia gravis
- have any other medical conditions
- are pregnant or plan to become pregnant. You should not take aspirin and extended-release dipyridamole capsules during pregnancy without first talking to your healthcare provider. Tell your healthcare provider right away if you become pregnant while taking aspirin and extended-release dipyridamole capsules.
- are breastfeeding or plan to breastfeed. Aspirin and extended-release dipyridamole capsules can pass into your milk. Talk to your healthcare provider about the best way to feed your baby if you take aspirin and extended-release dipyridamole capsules.

Tell your doctor you are taking aspirin and extended-release dipyridamole capsules if you are scheduled to have a stress test for your heart.

Tell your doctor about all the medicines you take, including prescription and non-prescription medicines, vitamins and herbal supplements. Aspirin and extended-release dipyridamole capsules and other medicines may affect each other causing side effects. Aspirin and extended-release dipyridamole capsules may affect the way other medicines work, and other medicines may affect how aspirin and extended-release dipyridamole capsules works.

Especially tell your healthcare provider if you take:

- a medicine for high blood pressure, irregular heart beat, or heart failure
- acetazolamide [Diamox®]
- any blood thinner medicines
- warfarin sodium [Coumadin®, Jantoven®]
- a heparin medicine
- anagrelide [Agrylin®]
- a seizure medicine
- a medicine for Alzheimer's disease
- a water pill
- methotrexate sodium [Trexall®]
- aspirin or a non-steroidal anti-inflammatory drug (NSAIDs). You should not take NSAIDs during treatment with aspirin and extended-release dipyridamole capsules. Using these medicines with aspirin and extended-release dipyridamole capsules can increase your risk of bleeding.
- a medicine for diabetes
- probenecid [Probalan®, Col-Probenecid®]

Ask your healthcare provider or pharmacist if you are not sure if your medicine is one that is listed above.

Know the medicines you take. Keep a list of them and show your healthcare provider and pharmacist when you get a new medicine.

How should I take Aspirin and Extended-Release Dipyridamole Capsules?

- Take aspirin and extended-release dipyridamole capsules exactly as prescribed. Your healthcare provider will tell you how many aspirin and extended-release dipyridamole capsules to take and when to take them.
- Headaches are not uncommon when you first start taking aspirin and extended-release dipyridamole capsules, but often lessen as treatment continues. Tell your healthcare provider if you have a severe headache. Your healthcare provider may change the instructions for taking aspirin and extended-release dipyridamole capsules.
- Swallow aspirin and extended-release dipyridamole capsules whole. Do not crush or chew the capsules.
- You can take aspirin and extended-release dipyridamole capsules with or without food.
- If you miss a dose, take your next dose at the usual time. Do not take two doses at one time.
- If you take more aspirin and extended-release dipyridamole capsules (overdose) than prescribed, call your healthcare provider or Poison Control Center, or get emergency help right away.

Symptoms of an overdose of Aspirin and Extended-Release Dipyridamole Capsules include:

- a warm feeling or flushing
- sweating
- restlessness
- weakness or dizziness
- a fast heart rate
- ringing in the ears

What should I avoid while using Aspirin and Extended-Release Dipyridamole Capsules?

- heavy alcohol use. People who drink three or more alcoholic drinks every day have a higher risk of bleeding during treatment with aspirin and extended-release dipyridamole capsules, because it contains aspirin.

What are the possible side effects of Aspirin and Extended-Release Dipyridamole Capsules?

Aspirin and extended-release dipyridamole capsules may cause serious side effects, including:

- increased risk of bleeding. You may bleed more easily during aspirin and extended-release dipyridamole capsules treatment, and it may take longer than usual for bleeding to stop. This can include:
  - bleeding into your brain (intracranial hemorrhage). This can be a medical emergency. Get medical help right away if you have any of these symptoms while taking aspirin and extended-release dipyridamole capsules:
    - severe headache with drowsiness
    - confusion or memory change
    - pass out (become unconscious)
  - bleeding in your stomach or intestine.
    - stomach pain
    - heartburn or nausea
    - vomiting blood or vomit looks like "coffee grounds"
    - red or bloody stools
    - black stools that look like tar
- new or worsening chest pain in some people with heart disease. Tell your healthcare provider if you have new chest pain or have any change in your chest pain during treatment with aspirin and extended-release dipyridamole capsules.
- liver problems, including increased liver function tests and liver failure. Tell your healthcare provider if you have any of these symptoms of a liver problem while taking aspirin and extended-release dipyridamole capsules:
  - loss of appetite
  - pale colored stool
  - stomach area (abdomen) pain
  - yellowing of your skin or whites of your eyes
  - dark urine
  - itching

Call your healthcare provider right away if you have any of the symptoms listed above.

The most common side effects of Aspirin and Extended-Release Dipyridamole Capsules include:

- headache
- upset stomach
- diarrhea

These are not all the possible side effects of aspirin and extended-release dipyridamole capsules. Tell your healthcare provider or pharmacist if you have any side effect that bothers you or that does not go away.

Call your healthcare provider for medical advice about side effects. You may report side effects to FDA at 1-800-FDA-1088.

How should I store Aspirin and Extended-Release Dipyridamole Capsules?

- Store aspirin and extended-release dipyridamole capsules at room temperature 59ºF to 86ºF (15ºC to 30ºC).
- Keep aspirin and extended-release dipyridamole capsules dry.

Keep aspirin and extended-release dipyridamole capsules and all medicines out of the reach of children.

General information about Aspirin and Extended-Release Dipyridamole Capsules

Medicines are sometimes prescribed for purposes other than those listed in the Patient Information. Do not use aspirin and extended-release dipyridamole capsules for a condition for which it was not prescribed. Do not give aspirin and extended-release dipyridamole capsules to other people, even if they have the same symptoms that you have. It may harm them.

This Patient Information summarizes the most important information about aspirin and extended-release dipyridamole capsules. If you would like more information, talk with your healthcare provider. You can ask your pharmacist or healthcare provider for information about aspirin/extended-release dipyridamole capsules that is written for health professionals.

For more information, go to www.glenmarkpharma-us.com or call Glenmark Pharmaceuticals Inc., USA at 1 (888) 721-7115 or FDA at 1-800-FDA-1088.

What are the ingredients in Aspirin and Extended-Release Dipyridamole Capsules?

Active Ingredients: dipyridamole in an extended-release form and aspirin

Inactive Ingredients: acacia milled powder, eudragit S-100, glyceryl behenate, hydroxy propyl methyl cellulose phthalate HP-55, hypromellose, hypromellose E3LV, hypromellose E50LV, lactose monohydrate, microcrystalline cellulose, micronized talc, povidone K 30, silicon dioxide, talc, tartatic acid pellets and triacetin.

Each capsule shell contains FD & C blue 1, FD & C red 3, FD & C red 40, FD & C yellow 6, gelatin, iron oxide yellow, sodium lauryl sulphate and titanium dioxide.

The imprinting ink contains black iron oxide, potassium hydroxide, and shellac.

All trademarks are the property of their respective owners.

Distributed by:

Glenmark Pharmaceuticals Inc., USA

Elmwood Park, NJ 07407

Questions? 1 (888) 721-7115

www.glenmarkpharma-us.com

September 2025

PACKAGE/LABEL PRINCIPAL DISPLAY PANEL

Aspirin and Extended-Release Dipyridamole Capsules

25 mg/200 mg – 60 Capsule

NDC 68462-405-60